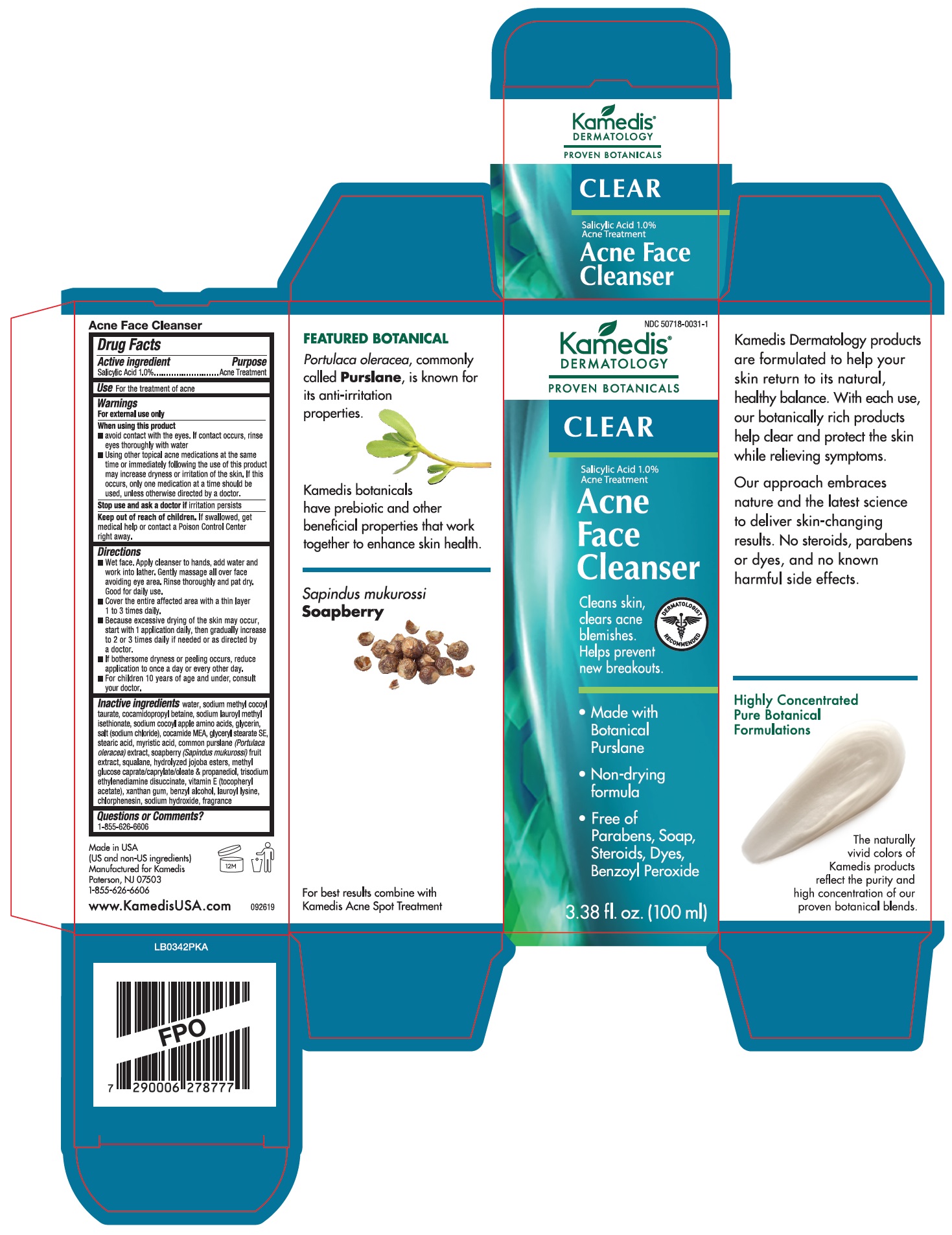 DRUG LABEL: Clear Acne Face Cleanser
NDC: 50718-0031 | Form: LIQUID
Manufacturer: Kamedis
Category: otc | Type: HUMAN OTC DRUG LABEL
Date: 20240207

ACTIVE INGREDIENTS: SALICYLIC ACID 14.4 mg/1 mL
INACTIVE INGREDIENTS: BENZYL ALCOHOL; PURSLANE; CHLORPHENESIN; GLYCERIN; PROPANEDIOL; WATER; XANTHAN GUM; SODIUM HYDROXIDE; SQUALANE; COCAMIDOPROPYL BETAINE; GLYCERYL STEARATE SE; COCO MONOETHANOLAMIDE; LAUROYL LYSINE; MYRISTIC ACID; SODIUM CHLORIDE; SAPINDUS MUKOROSSI FRUIT; SODIUM LAUROYL METHYL ISETHIONATE; SODIUM METHYL COCOYL TAURATE; STEARIC ACID; EDETATE SODIUM; TRISODIUM ETHYLENEDIAMINE DISUCCINATE; .ALPHA.-TOCOPHEROL ACETATE; HYDROLYZED JOJOBA ESTERS (ACID FORM); SODIUM COCOYL APPLE AMINO ACIDS; METHYL GLUCOSE

Clear Acne Face Cleanser

Drug Facts

Active ingredient

Salicylic Acid 1.0%

Purpose

Acne Treatment

Use

- For the treatment of acne

Warnings

For external use only

When using this product

- avoid contact with the eyes. If contact occurs, rinse eyes thoroughly with water
- using other topical acne medications at the same time or immediately following the use of this product may increase dryness or irritation of the skin. If this occurs, only one medication at a time should be used, unless otherwise directed by a doctor.

Stop use and ask a doctor

- if irritation persists

Keep out of reach of children

- If swallowed, get medical help or contact a Poison Control Center right away.

Directions

- Wet face. Apply cleanser to hands, add water and work into lather. Gently massage all over face avoiding eye area. Rinse thoroughly and pat dry. Good for daily use.
- Cover the entire affected area with a thin layer 1 to 3 times daily.
- Because excessive drying of the skin may occur, start with 1 application daily, then gradually increase to 2 or 3 times daily if needed or as directed by a doctor.
- If bothersome dryness or peeling occurs, reduce application to once a day or every other day.
- For children under 10 years of age and under, consult your doctor.

Inactive Ingredients

water, sodium methyl cocoyl taurate, cocamidopropyl betaine, sodium lauroyl methyl isethionate, sodium cocoyl apple amino acids, glycerin, salt (sodium chloride), cocamide MEA, glyceryl stearate SE, stearic acid, myristic acid, common purslane (Portulaca oleracea) extract, soapberry (Sapindus mukurossi) fruit extract, squalane, hydrolyzed jojoba esters, methyl glucose caprate/caprylate/oleate & propanediol, trisodium ethylenediamine disuccinate, vitamin E (tocopheryl acetate), xanthan gum, benzyl alcohol, lauroyl lysine, chlorphenesin, sodium hydroxide, fragrance

Questions or Comments?

1-855-626-6606

Made in USA
(US and non-US ingredients)
Manufactured for Kamedis
Paterson, NJ 07503
1-855-626-6606

www.KamedisUSA.com